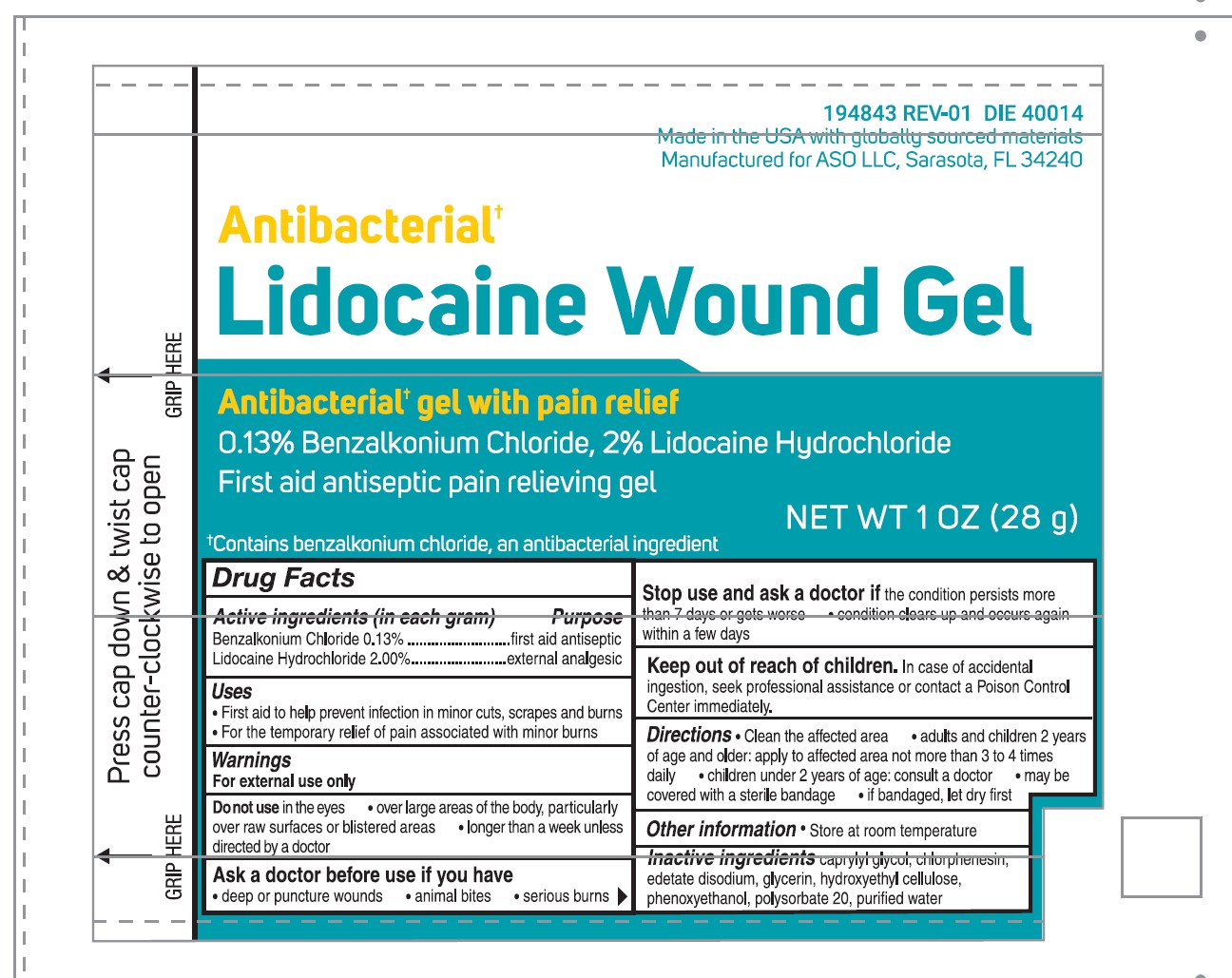 DRUG LABEL: Antibacterial Lidocaine Wound Gel
NDC: 59898-950 | Form: GEL
Manufacturer: Water-Jel Technologies, LLC
Category: otc | Type: HUMAN OTC DRUG LABEL
Date: 20251231

ACTIVE INGREDIENTS: LIDOCAINE HYDROCHLORIDE 2 g/100 mL; BENZALKONIUM CHLORIDE 0.13 g/100 mL
INACTIVE INGREDIENTS: CAPRYLYL GLYCOL; EDETATE DISODIUM; HYDROXYETHYL CELLULOSE, UNSPECIFIED; WATER; GLYCERIN; PHENOXYETHANOL; POLYSORBATE 20; CHLORPHENESIN

Antibacterial Lidocaine Wound Gel

Active ingredients (in each gram)

Benzalkonium Chloride 0.13%

Lidocaine Hydrochloride 2.00%

Purpose

first aid antiseptic

external analgesic

Uses

First aid to help prevent infection in minor cuts, scrapes and burns

For the temporary relief of pain associated with minor burns

Warnings

For external use only

Do not use

in the eyes

over large areas of the body, particularly over raw surfaces or blistered areas

longer than a week unless directed by a doctor

Ask a doctor before use if you have

deep or puncture wounds

animal bites

serious burns

Stop use and ask a doctor if

the condition persists more than 7 days or gets worse

Condition clears up and occurs again within a few days

Keep out of reach of children

In case of accidental ingestion, seek professional assistance or contact a Poison Control Center immediately.

Directions

clean the affected area

adults and children 2 years of age and older:

apply to affected area not more than 3 to 4 times daily

children under 2 years of age: consult a doctor

may be covered with a sterile bandage

if bandaged, let dry first

Other information

Store at room temperature

Inactive ingredients

caprylyl glycol, chlorphenesin, edetate disodium, glycerin, hydroxyethyl cellulose, phenoxyethanol, polysorbate 20, purified water